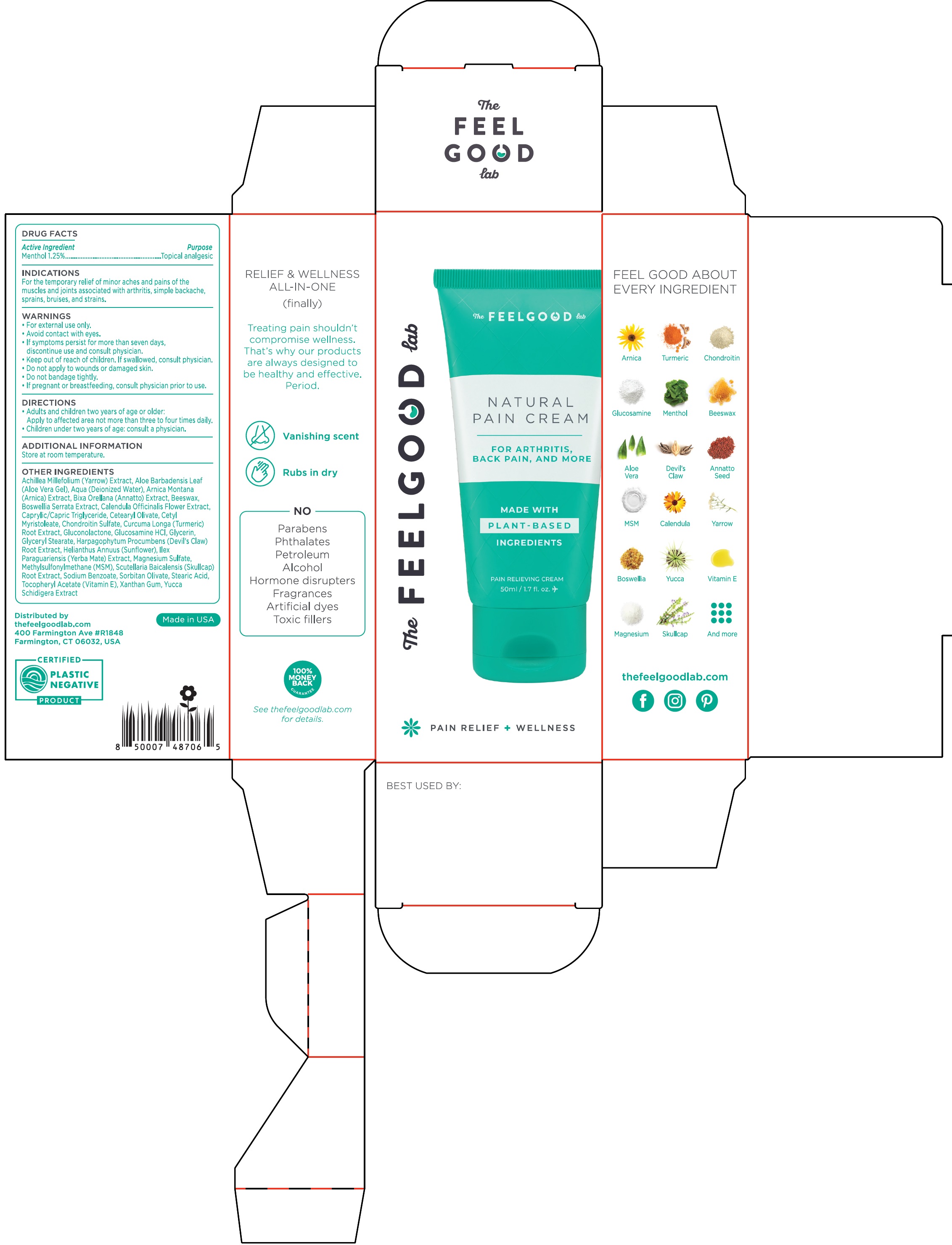 DRUG LABEL: FEELGOOD LAB Natural Pain Cream
NDC: 70554-229 | Form: CREAM
Manufacturer: The Feel Good Lab, LLC
Category: otc | Type: HUMAN OTC DRUG LABEL
Date: 20231110

ACTIVE INGREDIENTS: MENTHOL 12.5 mg/1 mL
INACTIVE INGREDIENTS: ACHILLEA MILLEFOLIUM WHOLE; ALOE VERA LEAF; WATER; ARNICA MONTANA FLOWER; ANNATTO; YELLOW WAX; INDIAN FRANKINCENSE; CALENDULA OFFICINALIS FLOWER; MEDIUM-CHAIN TRIGLYCERIDES; CETEARYL OLIVATE; CETYL MYRISTOLEATE; CHONDROITIN SULFATE (BOVINE); TURMERIC; GLUCONOLACTONE; GLUCOSAMINE HYDROCHLORIDE; GLYCERIN; GLYCERYL MONOSTEARATE; HARPAGOPHYTUM PROCUMBENS ROOT; HELIANTHUS ANNUUS FLOWERING TOP; ILEX PARAGUARIENSIS LEAF; MAGNESIUM SULFATE, UNSPECIFIED FORM; DIMETHYL SULFONE; SCUTELLARIA LATERIFLORA WHOLE; SODIUM BENZOATE; SORBITAN OLIVATE; STEARIC ACID; .ALPHA.-TOCOPHEROL ACETATE; XANTHAN GUM; YUCCA SCHIDIGERA WHOLE

FEELGOOD LAB Natural Pain Cream

Active Ingredient

Menthol 1.25%

Purpose

Topical analgesic

INDICATIONS

For the temporary relief of minor aches and pains of the muscles and joints associated with arthritis, simple backache, sprains, bruises, and strains.

WARNINGS:

- For external use only.
- Avoid contact with eyes.
- If symptoms persist for more than seven days, discontinue use and consult a physician.

Keep out of reach of children.

- If swallowed, consult physician.
- Do not apply to wounds or damages skin.
- Do not bandage tightly.

If pregnant or breastfeeding,

- consult physician prior to use.

DIRECTIONS

- Adults and children two years of age on older: Apply to affected area not more than three to four times daily.
- Children under two years of age: consult a physician.

ADDITIONAL INFORMATION

Store at room temperature.

OTHER INGREDIENTS

Achillea Mellefolim (Yarrow) Extract, Aloe Barbadensis Leaf (Aloe Vera Gel), Aqua (Deionized Water), Arnica Montana (Arnica) Extract, Bixa Orellana (Annatto) Extract, Beeswax, Boswellia Serrata Extract,Calendula Officinalis Flower Extract, Caprylic/Capric Triglyceride, Cetearyl Olivate, Cetyl Myristoleate, Chondroitin Sulfate, Curcuma Longa (Turmeric) Root Extract, Gluconolactone, Glucosamine HCL, Glycerin, Glyceryl Stearate, Harpagophytum Procumbens (Devil's Claw) Root Extract, Helianthus Annuus (Sunflower), Ilex Paraguariensis (Yerba Mate) Extract, Magnesium Sulfate, Methylsulfonylmethane (MSM), Scutellaria Baicalensis (Skullcap) Root Extract, Sodium Benzoate, Sorbitan Olivate, Stearic Acid, Tocopheryl Acetate (Vitamin E), Xanthan Gum, Yucca Schidigera Extract